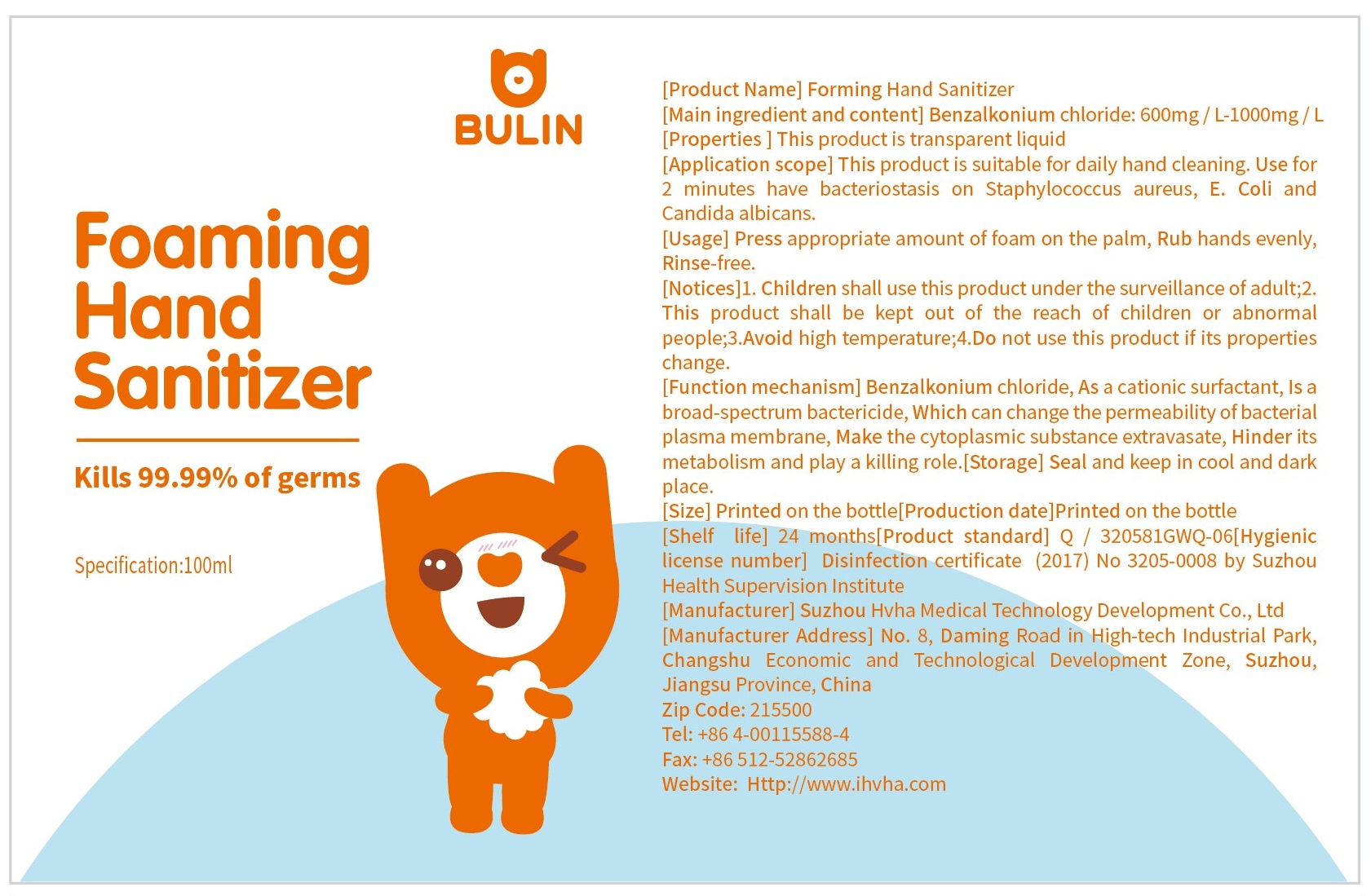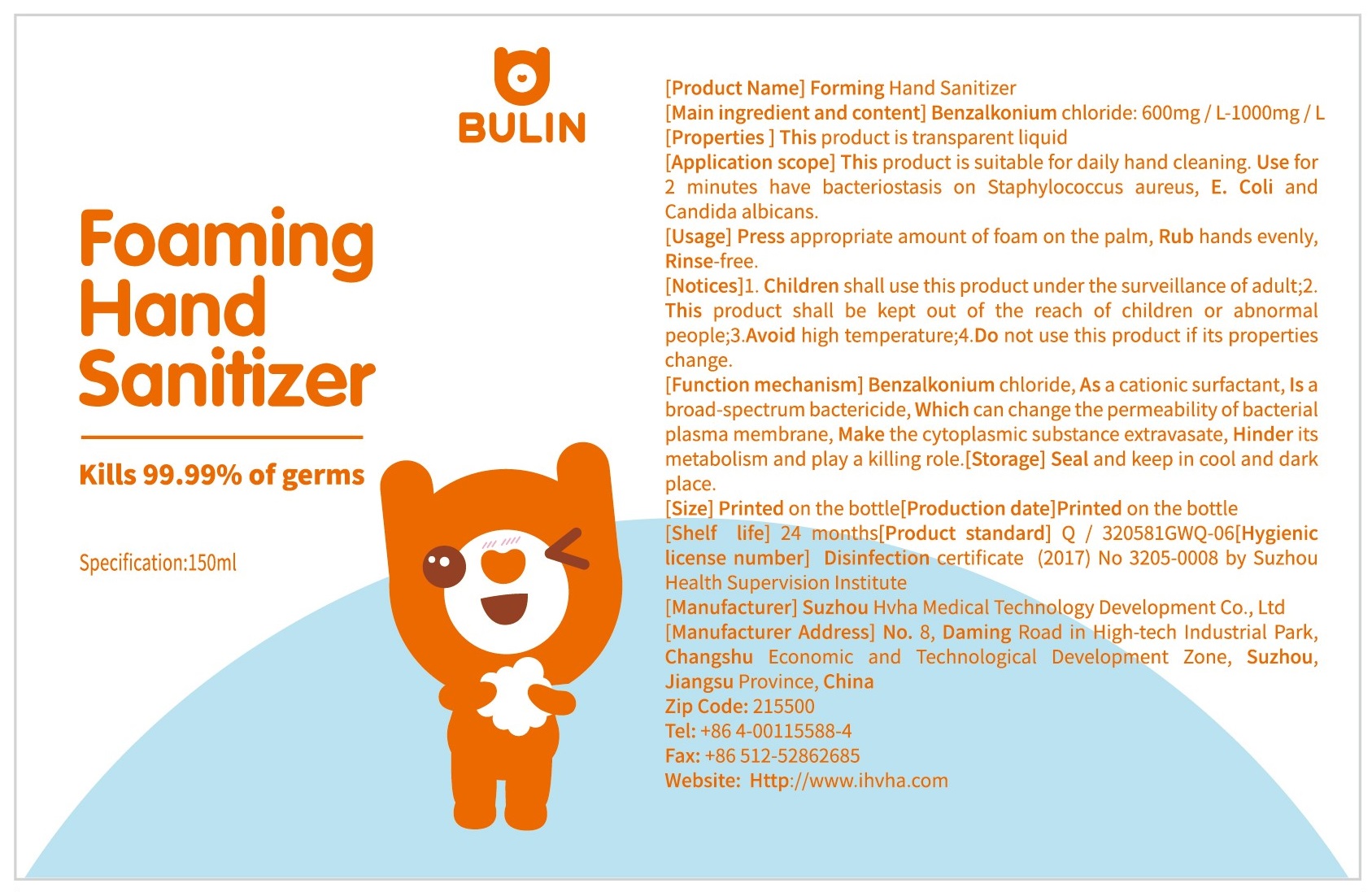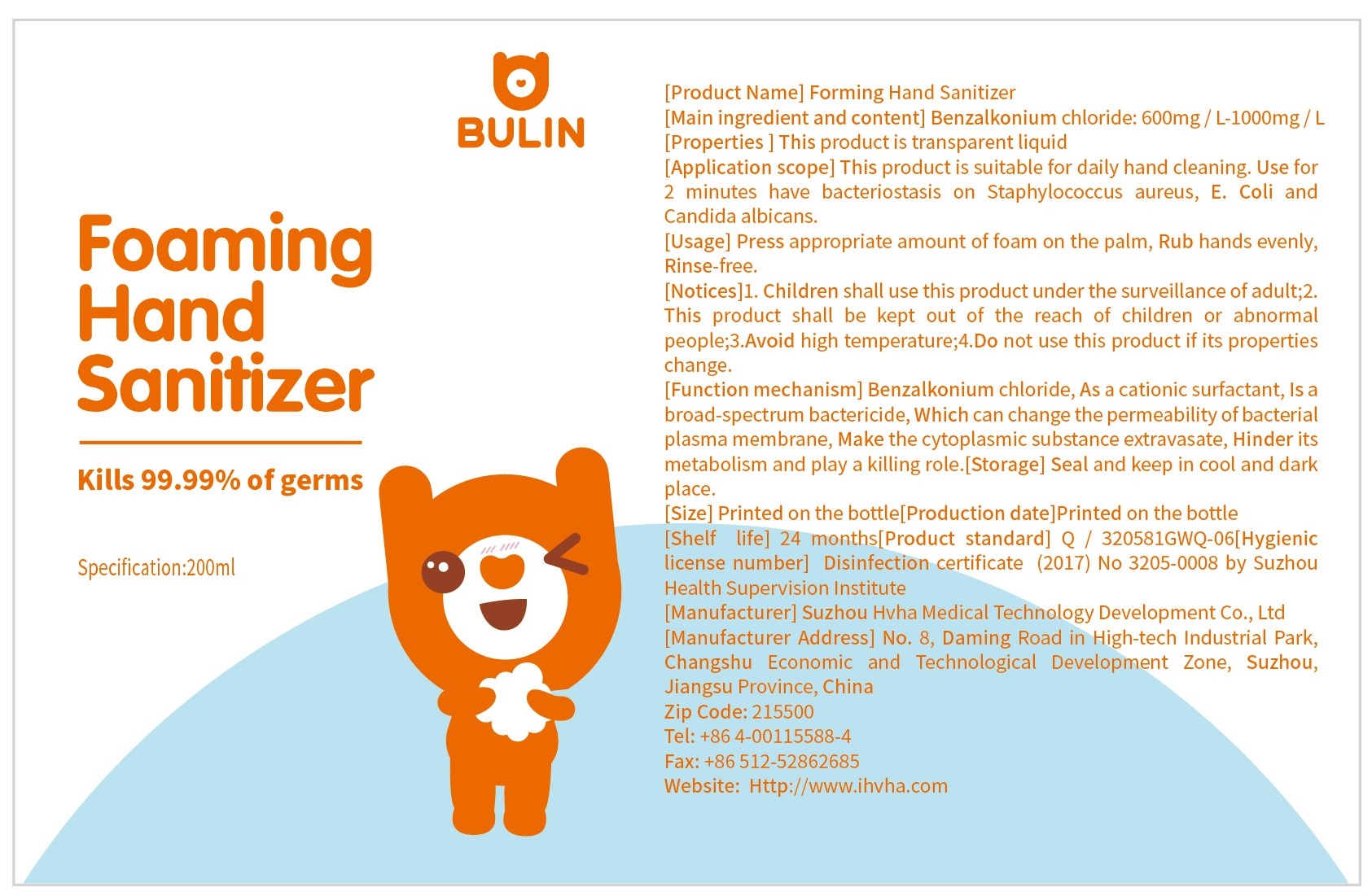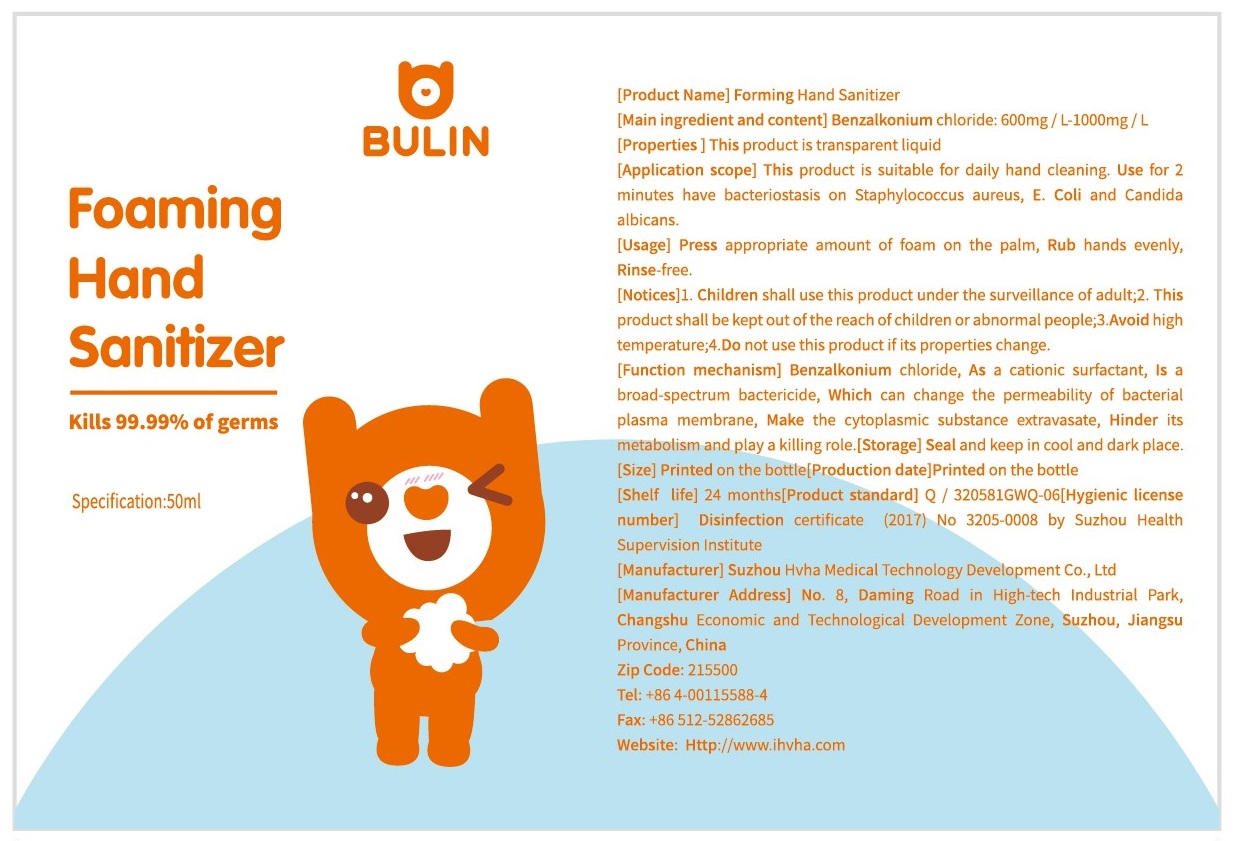 DRUG LABEL: Foaming Hand Sanitizer
NDC: 77263-002 | Form: LIQUID
Manufacturer: Suzhou HVHA Medical Technology Development Co.,Ltd.
Category: otc | Type: HUMAN OTC DRUG LABEL
Date: 20211228

ACTIVE INGREDIENTS: BENZALKONIUM CHLORIDE 0.8 mg/1 mL
INACTIVE INGREDIENTS: WATER; GLYCERIN; POLYSORBATE 80

Foaming Hand Sanitizer

Main ingredients and content

Benzalkonium chloride: 600mg/L-1000mg/L

Properties

This product is transparent liquid

Application scope

This product is suitable for daily hand cleaning. Use for 2 minutes have bacteriostasis on Staphylococcus aureus, E. Coli and Candida albicans.

Usage

Press appropriate amount of foam on the palm, rub hands evenly, rinse-free.

Notices

Children shall use this product under the surveillance of adult.

This product shall be kept out of the reach of children or abnormal people.

WARNINGS

Avoid high temperature.

Do not use this product if its properties change.

Function mechanism

Benzalkonium chloride, as a cationic surfactant, is a broad-spectrum bactericide, which can change the permeability of bacterial plasma membrane, make the cytoplasmic substance extravasate, hinder its metabolism and play a killing role.

Storage

Seal and keep in cool and dark place

Shelf life: 24 months

Inactive ingredients

Water, Glycerin and Polysorbate 80

Purpose

Hand sanitizing